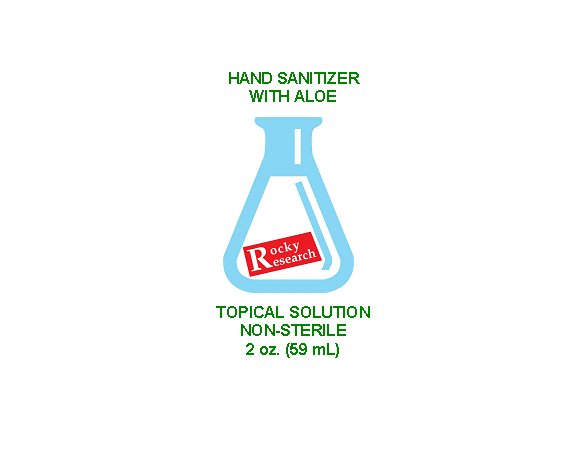 DRUG LABEL: Rocky Research Hand Sanitizer
NDC: 77509-065 | Form: GEL
Manufacturer: Rocky Research
Category: otc | Type: HUMAN OTC DRUG LABEL
Date: 20200518

ACTIVE INGREDIENTS: ISOPROPYL ALCOHOL 65 mL/100 mL
INACTIVE INGREDIENTS: ALOE VERA LEAF; CARBOMER 940; TROLAMINE; GLYCERIN 1.4 mL/100 mL; HYDROGEN PEROXIDE 0.12 mL/100 mL; WATER

The hand sanitizer is manufactured using only the following United States Pharmacopoeia (USP) grade ingredients in the preparation of the product (percentage in final product formulation) consistent with World Health Organization (WHO) recommendations:

1. Isopropyl Alcohol (65%, v/v) in an aqueous solution denatured according to Alcohol and Tobacco Tax and Trade Bureau regulations in 27 CFR part 20.
2. Glycerin (1.4% v/v).
3. Hydrogen peroxide (0.12% v/v).
4. Distilled Water.
5. Aloe Bardensi powder
6. Carbomer 940
7. Triethanolamine
8. Essential oil

Active Ingredient(s)

Isopropyl Alcohol 65% v/v. Purpose: Antiseptic

Purpose

Antiseptic, Hand Sanitizer

Use

Hand Sanitizer to help reduce bacteria that potentially can cause disease. For use when soap and water are not available.

Warnings

For external use only. Flammable. Keep away from heat or flame

Do not use

- in children less than 2 months of age
- on open skin wounds

When using this product keep out of eyes, ears, and mouth. In case of contact with eyes, rinse eyes thoroughly with water.
Stop use and ask a doctor if irritation or rash occurs. These may be signs of a serious condition.
Keep out of reach of children. If swallowed, get medical help or contact a Poison Control Center right away.

Stop use and ask a doctor if irritation or rash occurs. These may be signs of a serious condition.

Keep out of reach of children. If swallowed, get medical help or contact a Poison Control Center right away.

Directions

- Place enough product on hands to cover all surfaces. Rub hands together until dry.
- Supervise children under 6 years of age when using this product to avoid swallowing.

Other information

- Store between 15-30C (59-86F)
- Avoid freezing and excessive heat above 40C (104F)

Inactive ingredients

glycerin, hydrogen peroxide, distilled water, carbomer 940, triethanolamine, essential oi.

Package Label - Principal Display Panel

59 ml NDC: 77509-065-01